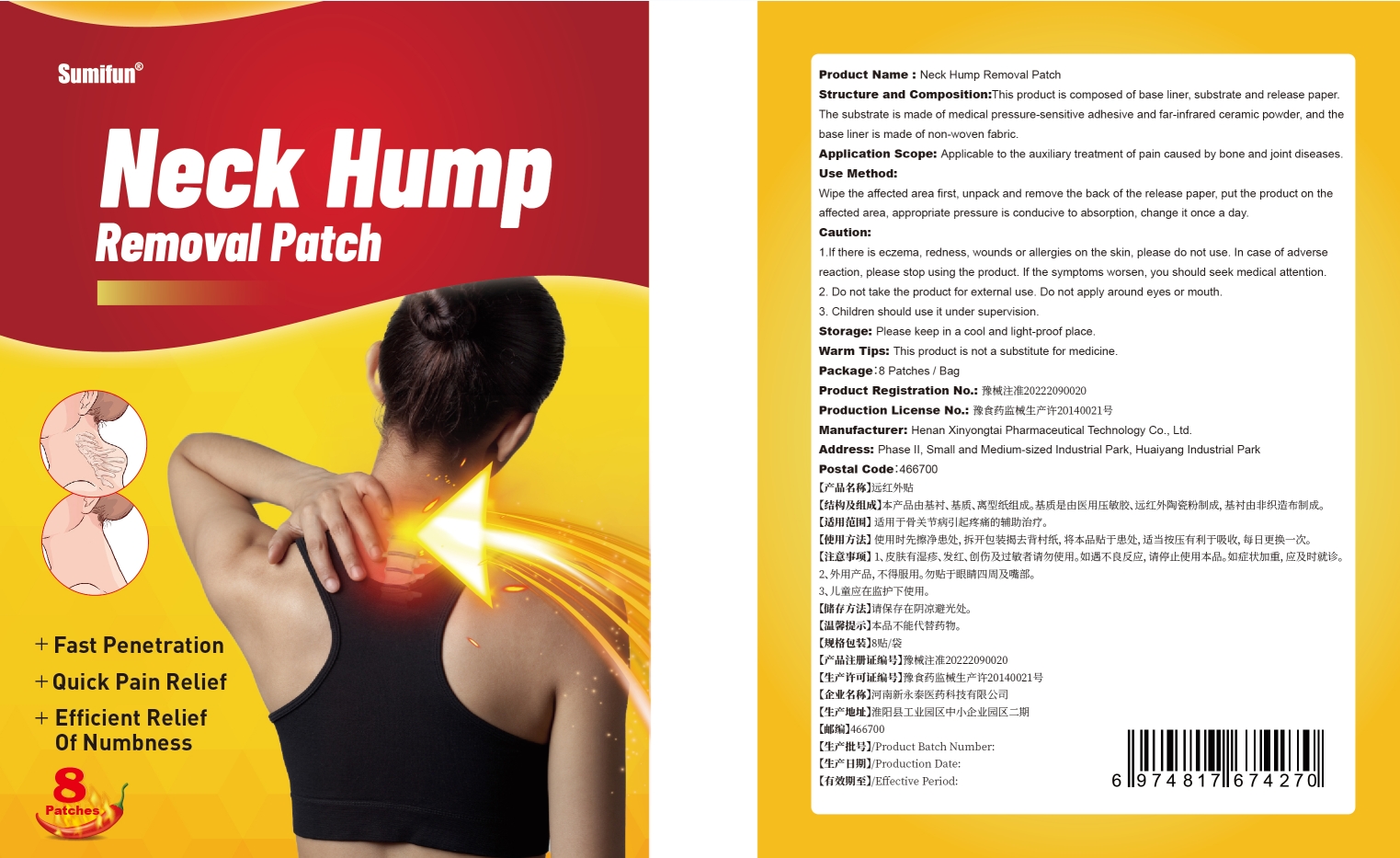 DRUG LABEL: Neck Hump Removal Patch
NDC: 83675-008 | Form: PATCH
Manufacturer: Guangzhou Hanhai Trading Co., Ltd
Category: otc | Type: HUMAN OTC DRUG LABEL
Date: 20230920

ACTIVE INGREDIENTS: IVERMECTIN 14 g/100 1
INACTIVE INGREDIENTS: LINERIXIBAT; 5-BROMO-4-CHLORO-3-INDOLYL PHOSPHATE; POWDERED CELLULOSE; DIETHYLENE GLYCOL ABIETATE

Active Ingredient

Ceramic Powder 21.0%

Purpose

Quick Pain Relief

Use

Neck Hump Removal Patch to help quick relieve pain

Warnings

For external use only. Do not take it internally.

Keep Out Of Reach Of Children
Prohibited for those with damaged skin.

Do not use

Product shall not be eat

When Using

Do not stick around eyes and mouth,This product cannot replace drugs.

Stop Use

In case of adverse reactions, please stop using this product.If the symptoms.

Ask Doctor

ask doctor in case of adverse reactions

Keep Oot Of Reach Of Children

Keep Out Of Reach Of Children

Directions

Take one piece of this product when needed, remove the waxpaper,

stick to the desired area and press the surrounding, replace it every day.

Children should be used under adult supervision.

Other information

Store the product in a cool, dry and well-ventilated place

Avoid direct sunlight

Inactive ingredients

base liner

substrate

release paper

pressure-sensitive adhesive